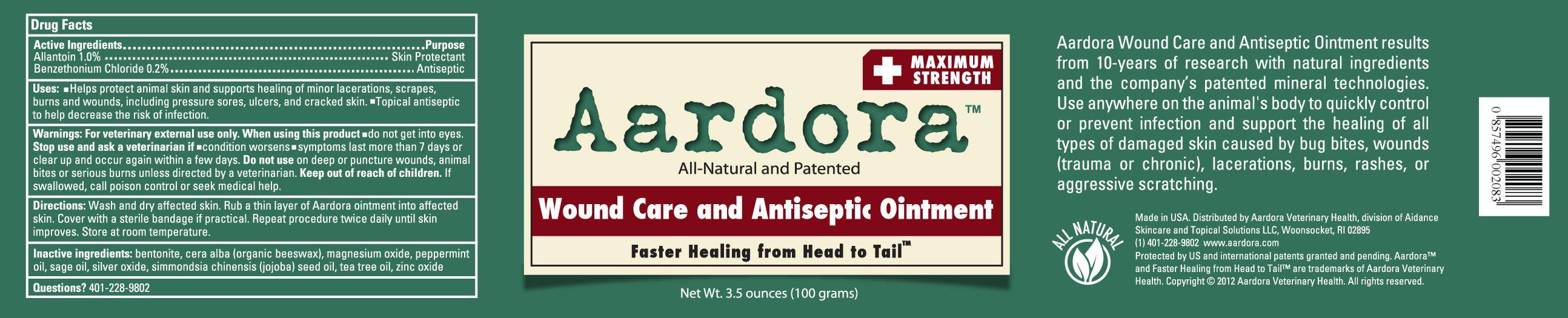 DRUG LABEL: Aardora Wound Care and Antiseptic
NDC: 24909-808 | Form: OINTMENT
Manufacturer: Aidance Skincare & Topical Solutions, LLC
Category: animal | Type: OTC ANIMAL DRUG LABEL
Date: 20121109

ACTIVE INGREDIENTS: ALLANTOIN 1.0 g/100 g; BENZETHONIUM CHLORIDE 0.2 g/100 g
INACTIVE INGREDIENTS: BENTONITE; JOJOBA OIL; MAGNESIUM OXIDE; PEPPERMINT OIL; SAGE OIL; SILVER OXIDE; TEA TREE OIL; WHITE WAX; ZINC OXIDE

Drug Facts

Active Ingredients

Allantoin 1.0%, Benzethonium Chloride 0.2%

Purpose

Allantoin - Skin Protectant

Benzethonium Chloride - Antiseptic

Uses

- Helps protect animal skin and supports healing of minor lacerations, scrapes, burns and wounds, including pressure sores, ulcers, and cracked skin.
- Topical antiseptic to help decrease the risk of infection.

Warnings

For veterinary external use only. When using this product - do not get into eyes.
Stop use and ask a veterinarian if - condition worsens - symptoms last more than 7 days or clear up and occur again within a few days.
Do not use on deep or puncture wounds, animal bites or serious burns unless directed by a veterinarian.

Directions

Wash and dry affected skin. Rub a thin layer of Aardora ointment into the affected skin. Cover with a sterile bandage if practical.
Repeat procedure twice daily until skin improves. Store at room temperature.

Inactive Ingredients

bentonite, cera alba (organic beeswax), magnesium oxide, peppermint oil, sage oil, silver oxide, simmondsia chinensis (jojoba) seed oil, tea tree oil, zinc oxide

Questions? 401-228-9802

Aardora Wound Care and Antiseptic Ointment results from 10-years of research with natural ingredients and the company's patented mineral technologies. Use anywhere on the animal's body to quickly control or prevent infection and support the healing of all types of damaged skin caused by bug bites, wounds (trauma or chronic), lacerations, burns, rashes, or aggressive scratching.
Made in USA. Distributed by Aardora Veterinary Health, a division of Aidance Skincare & Topical Solutions, LLC., Woonsocket, RI 02895.
(1) 401-228-9802 www.aardora.com
Protected by US and international patents granted and pending. Aardora™ and Faster Healing from Head to Tail™ are trademarks of Aardora Veterinary Health. Copyright (C) 2012 Aardora Veterinary Health. All rights reserved.

PRINCIPAL DISPLAY PANEL - 100g Jar

Aardora
Maximum Strength
All-Natural and Patented

Wound Care and Antiseptic Ointment
Faster Healing from Head to Tail™